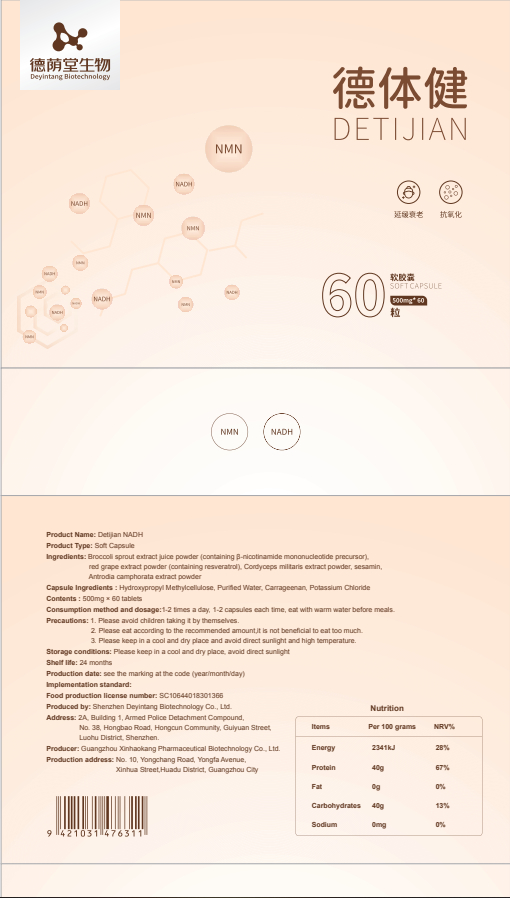 DRUG LABEL: Detijian NADH
NDC: 82570-006 | Form: CAPSULE
Manufacturer: Shenzhen Deyintang Biotechnology Co., Ltd.
Category: otc | Type: HUMAN OTC DRUG LABEL
Date: 20220221

ACTIVE INGREDIENTS: BROCCOLI SPROUT 10 g/100 g; MORINGA OLEIFERA LEAF 30 g/100 g; CORDYCEPS MILITARIS WHOLE 20 g/100 g; SESAMIN 22 g/100 g; TAIWANOFUNGUS CAMPHORATUS MYCELIUM 10 g/100 g
INACTIVE INGREDIENTS: HYPROMELLOSES; CARRAGEENAN; POTASSIUM CHLORIDE

ACTIVE INGREDIENT

BROCCOLI SPROUT EXTRACT (contain Sulforaphane, SFN),MORINGA OLEIFERA LEAF,Cordyceps militaris extract powder,sesamin,Antrodia camphorata extract powder

INACTIVE INGREDIENT

HYDROXYPROPYL METHYLCELLULOSE,CARRAGEENAN,POTASSIUM CHLORIDE

PURPOSE

health care

Please avoid children taking it by themselves.

Consumption method and dosage

1-2 times a day, 1-2 capsules each time, eat with warm water before meals.

INDICATIONS AND USAGE

Please eat according to the recommended amount,.it is not beneficial to eat too much

STORAGE AND HANDLING

Please keep in a cool and dry place, avoid direct sunlight

WARNINGS

1.Please avoid children taking it by themselves.
2.Please eat according to the recommended amount,.it is not beneficial to eat too much.

3.Please keep in a cool and dry place and avoid direct sunlight and high temperature.